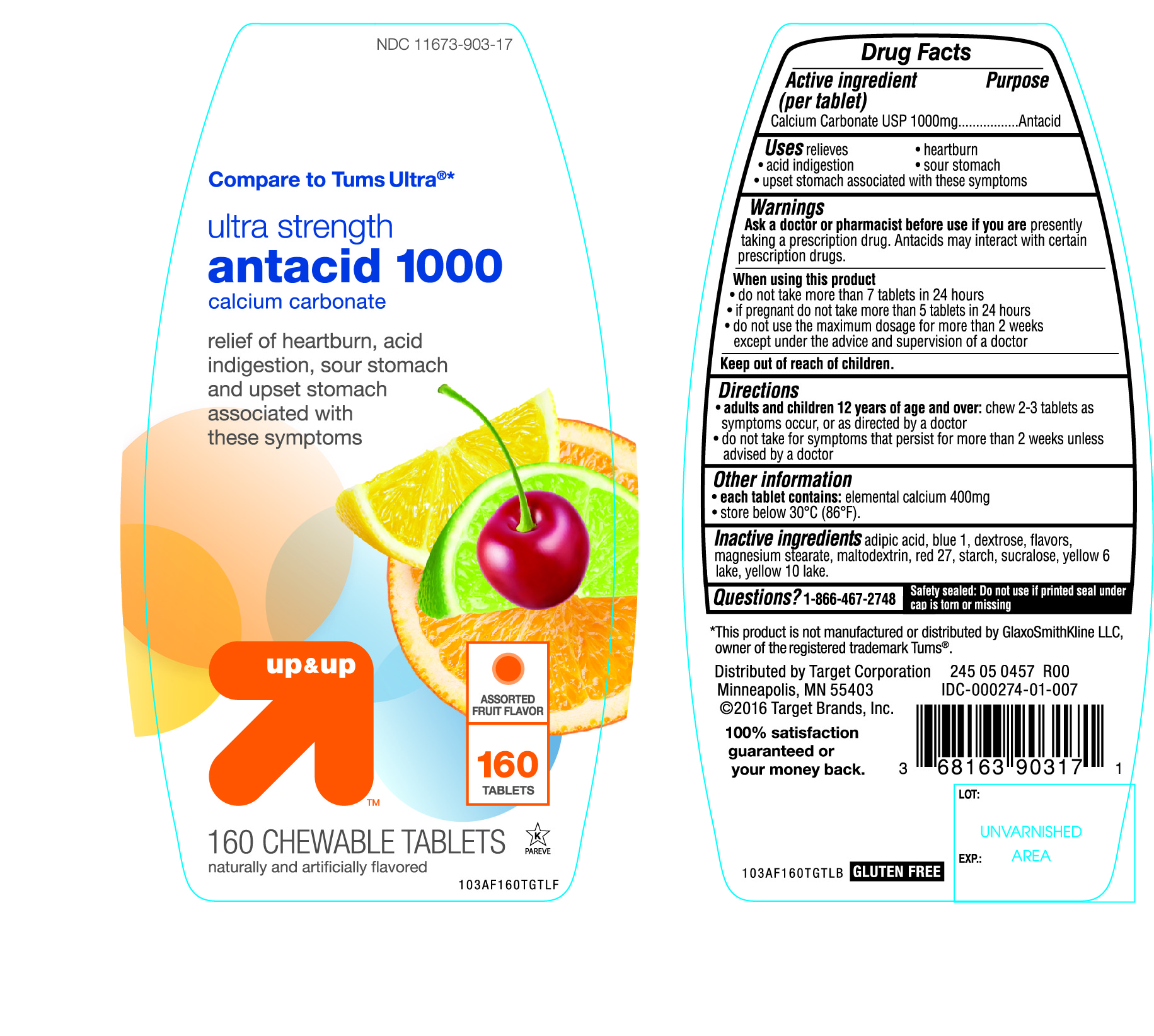 DRUG LABEL: up and up ultra strength antacid
NDC: 11673-903 | Form: TABLET, CHEWABLE
Manufacturer: Target Corporation
Category: otc | Type: HUMAN OTC DRUG LABEL
Date: 20150116

ACTIVE INGREDIENTS: CALCIUM CARBONATE 1000 mg/1 1
INACTIVE INGREDIENTS: ADIPIC ACID; FD&C BLUE NO. 1; DEXTROSE; MAGNESIUM STEARATE; MALTODEXTRIN; D&C RED NO. 27; STARCH, CORN; SUCRALOSE; FD&C YELLOW NO. 6; D&C YELLOW NO. 10

up and up ultra strength antacid 1000 chewable tablets

Active ingredient (per tablet)

Calcium Carbonate USP 1000mg

Purpose

Antacid

Uses

relieves

- heartburn
- acid indigestion
- sour stomach
- upset stomach associated with these symptoms

Warnings

Ask a doctor or pharmacist before use if you are presentlytaking a prescription drug. Antacids may interact with certain prescription drugs.

When using this product

do not take more than 7 tablets in 24 hours
if pregnant do not take more than 5 tablets in 24 hours
do not use the maximum dosage for more than 2 weeks except under the advice and supervision of a doctor.

Directions

adults and children 12 years of age and over: chew 2-3 tablets as symptoms occur, or as directed by a doctor
do not take for symptoms that persist for more than 2 weeks unless advised by a doctor

Other information

each tablet contains: elemental calcium 400mg
store below 30°C (86°F).

Inactive ingredients

adipic acid, blue 1, dextrose, flavors, magnesium stearate, maltodextrin, red 27, starch, sucralose, yellow 6 lake, yellow 10 lake.

Questions?

1-866-467-2748

Package/Label Principal Display Panel

NDC 11673-903-17

Compare to Tums Ultra®*

ultra strength

antacid 1000

calcium carbonate

relief of heartburn, acid indigestion ,sour stomach and upset stomach associated with these symptoms

ASSORTED FRUIT FLAVOR

160 TABLETS

160 CHEWABLE TABLETS

naturally and artificially flavored

245 05 0457 R00

IDC-000274-01-007

Distributed by

Target Corporation

Minneapolis, MN 55403

©2016 Target Brands, Inc.

*This product is not manufactured or distributed by GlaxoSmithKline LLC, owner of the registered trademark Tums®.

GLUTEN FREE

Safety sealed: Do not use if printed seal under cap is torn or missing

100% satisfaction guaranteed or your money back.